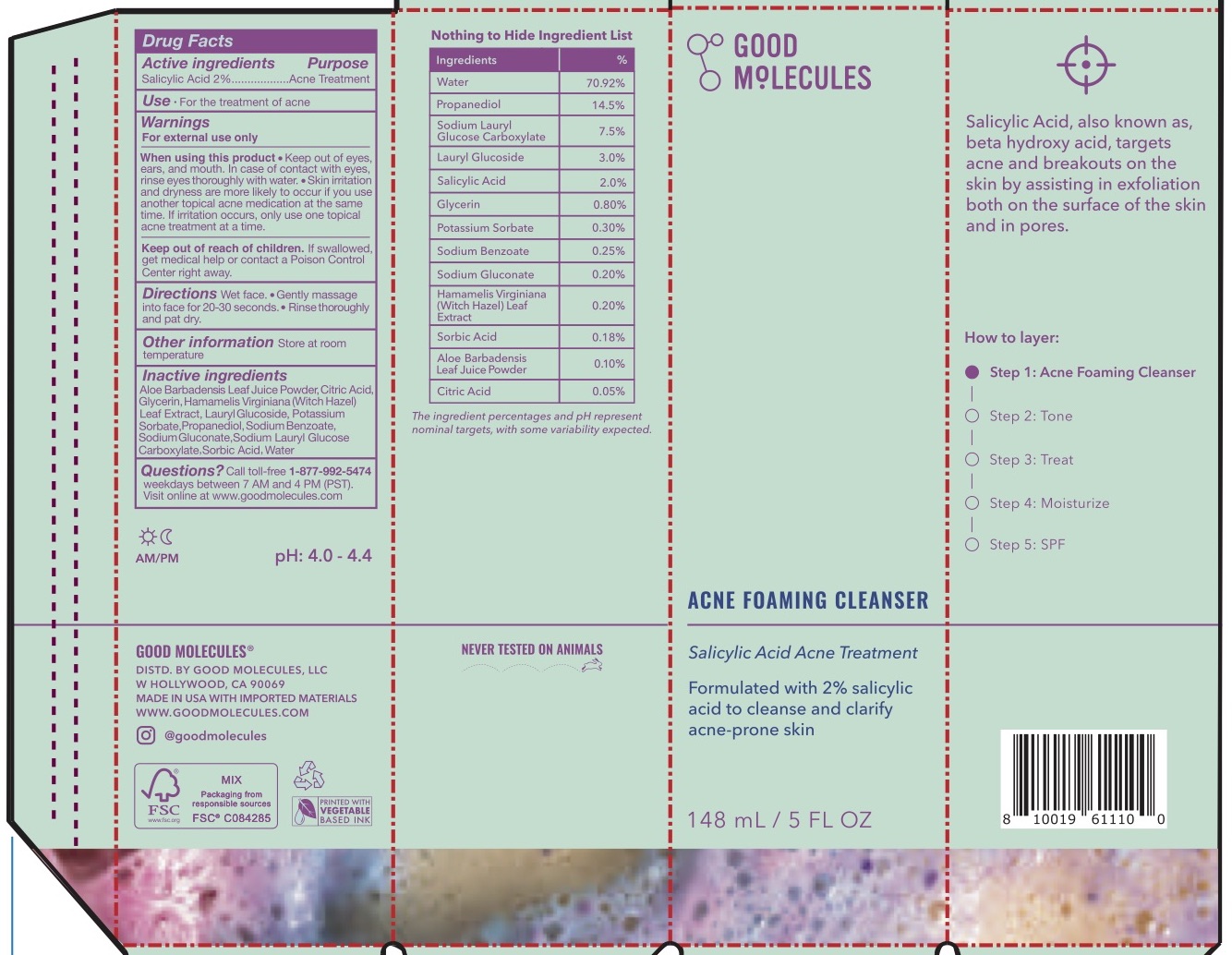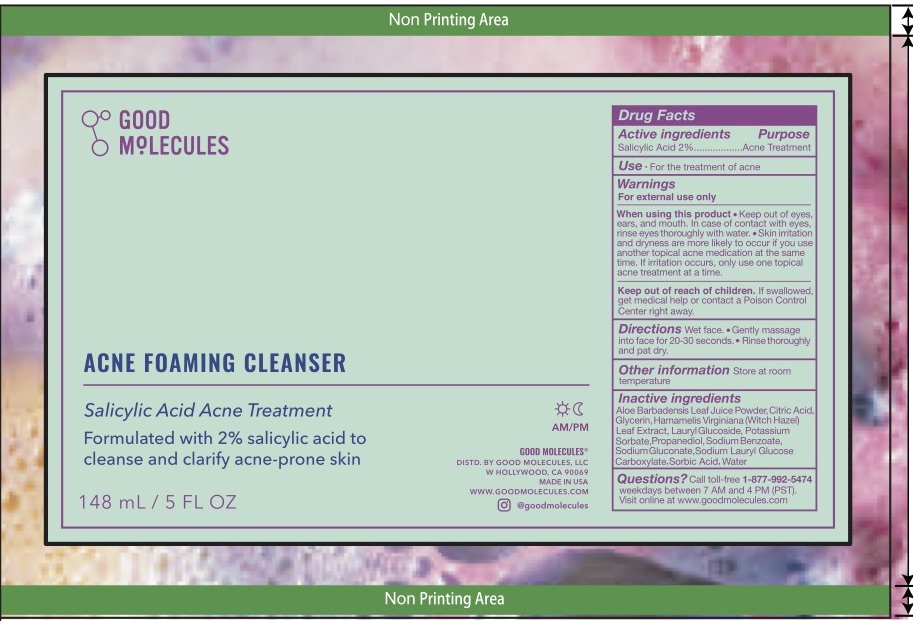 DRUG LABEL: Good Molecules Acne Foaming Cleanser
NDC: 82730-100 | Form: GEL
Manufacturer: Good Molecules
Category: otc | Type: HUMAN OTC DRUG LABEL
Date: 20240724

ACTIVE INGREDIENTS: SALICYLIC ACID 2 g/100 mL
INACTIVE INGREDIENTS: HAMAMELIS VIRGINIANA LEAF WATER; GLYCERIN; SODIUM LAURYL GLYCOL CARBOXYLATE; SODIUM BENZOATE; SORBIC ACID; SODIUM GLUCONATE; POTASSIUM SORBATE; LAURYL GLUCOSIDE; PROPANEDIOL; WATER; CITRIC ACID MONOHYDRATE; ALOE VERA LEAF

Good Molecules Acne Foaming Cleanser

Purpose

Acne treatment

Use

- For the treatment of acne

Active Ingredient

Salicylic Acid 2%

Directions

- Wet face
- Gently massage into face for 20-30 seconds.
- Rinse thoroughly and pat dry

Warnings

For external use only

Keep out of reach of children

If swallowed, get medical help or contact a poison control center immediately.

When using this product

Keep out of eyes, ears, and mouth. In case of contact with eyes, rinse eyes thoroughly with water. Skin irritation and dryness are more likely to occur if you use another topical acne medication at the same time. If irritation occurs, oinly use one topical acne medication at a time.

Inactive Ingredients

Aloe Barbadensis Leaf Juice Powder, Citric Acid, Glycerin, Hamamelis Virginiana (Witch Hazel) Leaf Extract, Lauryl Glucoside, Potassium Sorbate, Propanediol, Salicylic Acid (Synthetic), Sodium Benzoate, Sodium Gluconate (Natural), Sodium Lauryl Glucose Carboxylate Sorbic Acid, Water

Other Information

Store at room temperature

Questions?

Call toll-free 1-877-992-5474 weekdays between 7 AM and 4 PM (PST)